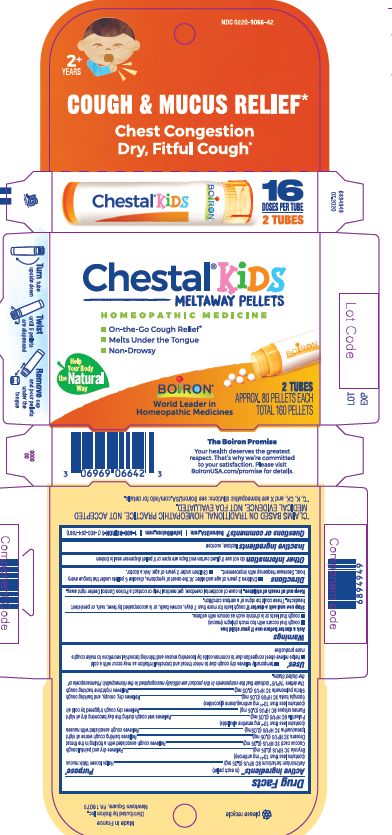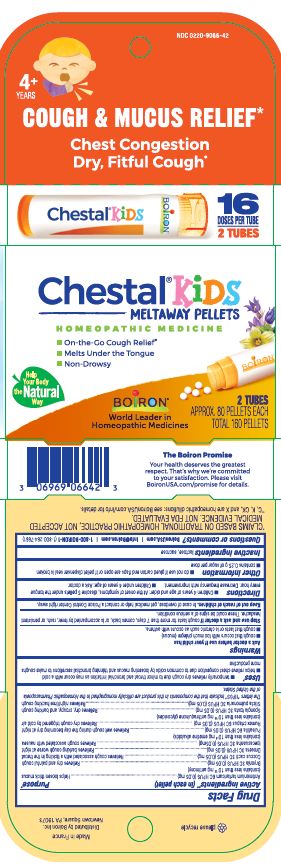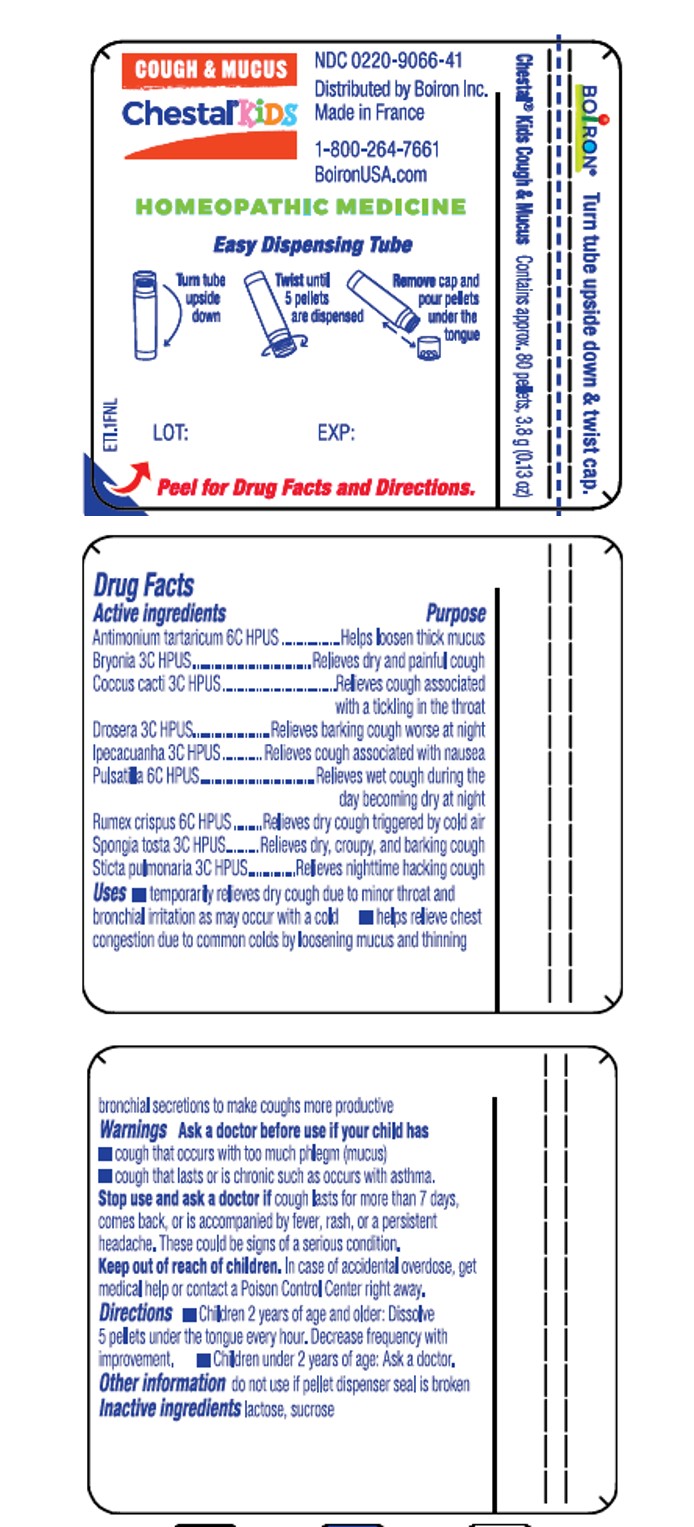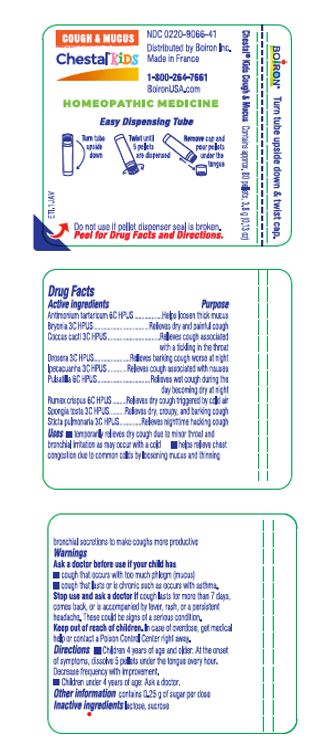 DRUG LABEL: Chestal Kids Pellets
NDC: 0220-9066 | Form: PELLET
Manufacturer: Boiron
Category: homeopathic | Type: HUMAN OTC DRUG LABEL
Date: 20240216

ACTIVE INGREDIENTS: SPONGIA OFFICINALIS SKELETON, ROASTED 3 [hp_C]/1 1; PULSATILLA VULGARIS 6 [hp_C]/1 1; BRYONIA ALBA ROOT 3 [hp_C]/1 1; DROSERA ROTUNDIFOLIA 3 [hp_C]/1 1; IPECAC 3 [hp_C]/1 1; LOBARIA PULMONARIA 3 [hp_C]/1 1; ANTIMONY POTASSIUM TARTRATE 6 [hp_C]/1 1; PROTORTONIA CACTI 3 [hp_C]/1 1; RUMEX CRISPUS ROOT 6 [hp_C]/1 1
INACTIVE INGREDIENTS: LACTOSE, UNSPECIFIED FORM; SUCROSE

Chestal Pellets Kids

Active ingredients** (in each pellet)

Antimonium tartaricum 6C HPUS (0.05 mg) (contains less than 10^-13 mg antimony)

Bryonia 3C HPUS (0.05mg)

Coccus cacti 3C HPUS (0.05mg)

Drosera 3C HPUS (0.05mg)

Ipecacuanha 3C HPUS (0.05mg) (contains less than 10^-8 mg emetine alkaloids)

Pulsatilla 6C HPUS (0.05mg)

Rumex crispus 6 HPUS (0.05mg) (contains less than 10^-16 mg anthraquinone glycosides)

Spongia tosta 3C HPUS (0.05mg)

Sticta pulmonaria 3C HPUS (0.05mg)

The letters "HPUS" indicate that the components in this product are officially monographed in the Homeopathic Pharmacopoeia of the United States.

Purpose*

Antimonium tartaricum 6C HPUS ... Helps loosen thick mucus

Bryonia 3C HPUS ... Relieves dry and painful cough

Coccus cacti 3C HPUS ... Relieves cough associated with a tickling in the throat

Drosera 3C HPUS ... Relieves barking cough worse at night

Ipecacuanha 3C HPUS ... Relieves cough associated with nausea

Pulsatilla 6C HPUS ... Relieves wet cough during the day becoming dry at night

Rumex crispus 6 HPUS ... Relieves dry cough triggered by cold air

Spongia tosta 3C HPUS ... Relieves dry, croupy, and barking cough

Sticta pulmonaria 3C HPUS ... Relieves nighttime hacking cough

Uses*

- temporarily relieves dry cough due to minor throat and bronchial irritation as may occur with a cold
- helps relieve chest congestion due to common colds by loosening mucus and thinning bronchial secretions to make coughs more productive

Ask a doctor before use if your child has

- cough that occurs with too much phlegm (mucus)
- cough that lasts or is chronic such as occurs with asthma.

Stop use and ask a doctor if cough lasts for more than 7 days, comes back, or is accompanied by fever, rash, or a persistent headache. These could be signs of a serious condition.

Keep out of reach of children. In case of overdose, get medical help or contact a Poison Control Center right away.

DOSAGE AND ADMINISTRATION

- Children 4 years of age and older: At the onset of symptoms, dissolve 5 pellets under the tongue every hour. Decrease frequency with improvement.
- Children under 4 years of age: Ask a doctor.

QUESTIONS

BoironUSA.com

Info@Boiron.com

1-800-BOIRON-1

(1-800-264-7661)

Distributed by Boiron, Inc.

Newtown Square, PA 19073

Made in France

INACTIVE INGREDIENT

lactose, sucrose

do not use if glue carton and flaps are open or if pellet dispenser seal is broken

contains 0.25 g of sugar per dose

Turn tube upside down & twist cap

Turn blue tube upside Twist until 5 pellets are dispensed

Remove cap and pour pellets under the tongue.

Tube - Contains approx. 80 pellets, 3.8 g (0.13 oz)

Box - Contains 2 tubes approx 80 pellets each total 160 pellets

On-the-Go Cough Relief*

Melts under the tongue

Non-Drowsy

Cough & Mucus Relief*

Chest Congestion Dry Fitful Cough*

*CLAIMS BASED ON TRADITIONAL HOMEOPATHIC PRACTICE, NOT ACCEPTED MEDICAL EVIDENCE. NOT FDA EVALUATED.
*C,K,CK, and X are homeopathic dilutions: see BoironUSA.com/info for details.